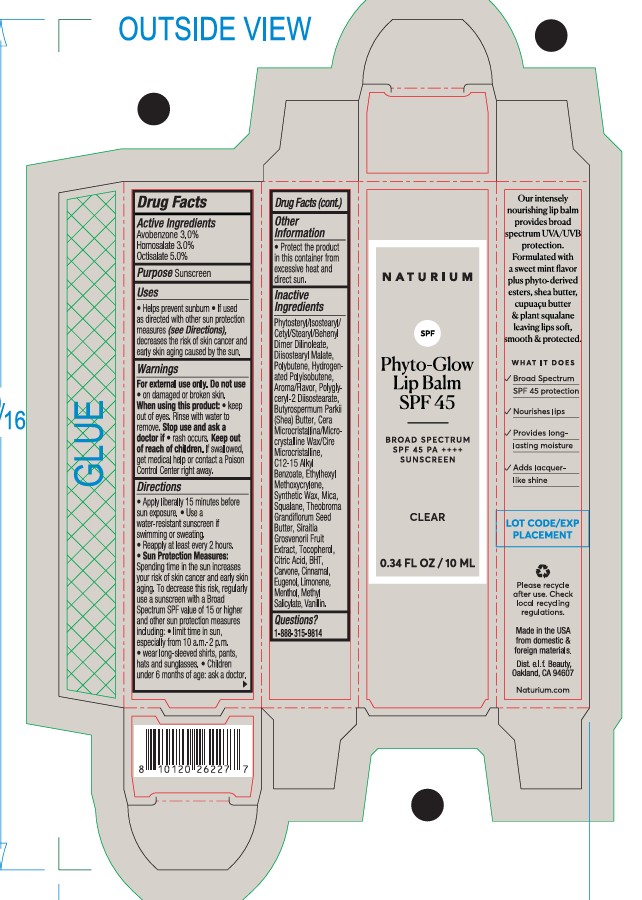 DRUG LABEL: Naturium Phyto-Glow Lip Balm SPF 45-Clear
NDC: 76354-135 | Form: CREAM
Manufacturer: e.l.f. Cosmetics, Inc.
Category: otc | Type: HUMAN OTC DRUG LABEL
Date: 20250609

ACTIVE INGREDIENTS: AVOBENZONE 30 mg/1 mL; HOMOSALATE 30 mg/1 mL; OCTISALATE 50 mg/1 mL
INACTIVE INGREDIENTS: POLYGLYCERYL-2 DIISOSTEARATE; SIRAITIA GROSVENORII FRUIT; CITRIC ACID; MICROCRYSTALLINE WAX; BHT; LIMONENE, (+)-; METHYL SALICYLATE; TOCOPHEROL; C12-15 ALKYL BENZOATE; THEOBROMA GRANDIFLORUM SEED BUTTER; PHYTOSTERYL/ISOSTEARYL/CETYL/STEARYL/BEHENYL DIMER DILINOLEATE; EUGENOL; VANILLIN; POLYBUTENE (1400 MW); CARVONE; MICA; HYDROGENATED POLYISOBUTENE (450 MW); SYNTHETIC WAX (1200 MW); ETHYLHEXYL METHOXYCRYLENE; BUTYROSPERMUM PARKII (SHEA) BUTTER; SQUALANE; FLAVOR SPICE MINT N&A110589; MENTHOL; DIISOSTEARYL MALATE; CINNAMAL

Naturium Phyto-Glow Lip Balm SPF 45

Active Ingredients

Avobenzone 3%

Homosalate 3%

Octisalate 5%

Purpose

Sunscreen

Uses

- Helps prevent sunburn
- If used as directed with other sun protection measures (see Directions) decreases the risk of skin cancer and early skin aging caused by the sun.

Warnings

For external use only.

Do not use

- on damaged or broken skin.

When using this product:

- keep out of eyes. Rinse with water to remove.

Stop use and ask a doctor if:

- rash occurs.

Keep out of reach of children.

- If swallowed, get medical help or contact a Poison Control Center right away.

Directions

- Apply liberally 15 minutes before sun exposure. Reapply at least every 2 hours.
- Use water resistant sunscreen if swimming or sweating.
- Sun Protection Measures: Spending time in the sun increases your risk of skin cancer and early skin aging. To decrease this risk, regularly use a sunscreen with a Board Spectrum SPF value of 15 or higher and other sun protection measures including: limit time in sun, especially from 10 a.m.-2 p.m., wear long-sleeved shirts, pants, hats and sunglasses. Children under 6 months of age: ask a doctor.

Other Information

- Protect the product in this container from excessive heat and direct sun.

Inactive Ingredients

Phytosteryl/Isostearyl/Cetyl/Stearyl/Behenyl Dimer Dilinoleate, Diisostearyl Malate, Polybutene, Hydrogenated Polyisobutene, Aroma/Flavor, Polyglyceryl-2 Diisostearate, Butyrospermum Parkii (Shea) Butter, Cera Microcristallina/Microcrystalline Wax/Cire Microcristalline, C12-15 Alkyl Benzoate, Ethylhexyl Methoxycrylene, Synthetic Wax, Mica, Squalane, Theobroma Grandiflorum Seed Butter, Siraitia Grosvenorii Fruit Extract, Tocopherol, Citric Acid, BHT, Carvone, Cinnamal, Eugenol, Limonene, Menthol, Methyl Salicylate, Vanillin.

Questions?

1-888-315-9814